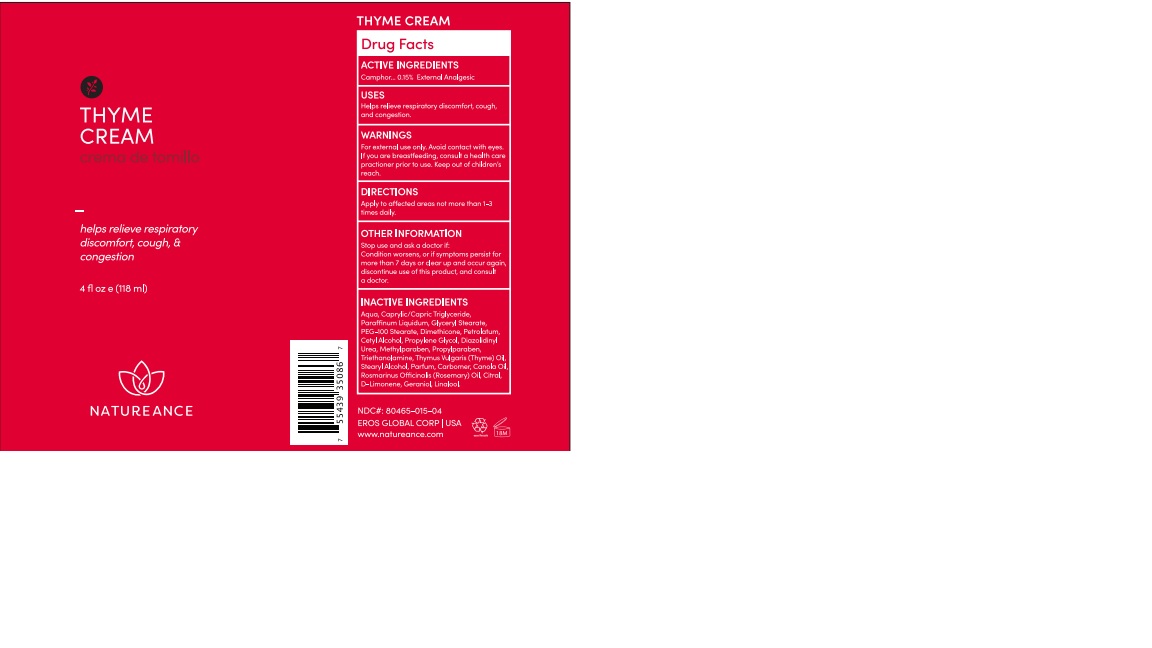 DRUG LABEL: CAMPHOR
NDC: 80465-015 | Form: CREAM
Manufacturer: EROS GLOBAL CORP
Category: otc | Type: HUMAN OTC DRUG LABEL
Date: 20220707

ACTIVE INGREDIENTS: CAMPHOR (NATURAL) 0.15 g/100 g
INACTIVE INGREDIENTS: GLYCERYL STEARATE/PEG-100 STEARATE; PROPYLPARABEN; THYMUS VULGARIS LEAF; ROSMARINUS OFFICINALIS FLOWERING TOP OIL; CITRAL; LINALOOL, (+)-; CETYL ALCOHOL; METHYLPARABEN; STEARYL ALCOHOL; CARBOMER 940; CANOLA OIL; LIMONENE, (+/-)-; GERANIOL; WATER; DIMETHICONE 1000; DIAZOLIDINYL UREA; PETROLATUM

80465-015-04

DOSAGE AND ADMINISTRATION

Apply to affected areas not more than 1-3 times daily.

WARNINGS

For external use only.
Avoid contact with eyes.
If you are breastfeeding, consult a health care practitioner prior to use.

INACTIVE INGREDIENT

Aqua, Caprylic/Capric Triglyceride, Paraffinum Liquidum, Glyceryl Stearate, PEG-100 Stearate, Dimethicone, Petrolatum, Cetyl Alcohol, Propylene Glycol, Diazolidinyl Urea, Methylparaben, Propylparaben, Triethanolamine, Thymus Vulgaris (Thyme) Oil, Stearyl Alcohol, Parfum, Carbomer, Canola Oil, Rosmarinus Officinalis (Rosemary) Oil, Citral, D-Limonene, Geraniol, Linalool.

INDICATIONS AND USAGE

Helps relieve respiratory discomfort, cough, and congestion.

Keep out of reach of the children.

PURPOSE

External Analgesic

ACTIVE INGREDIENT

Camphor……………………………………..………………….……... 0.15%